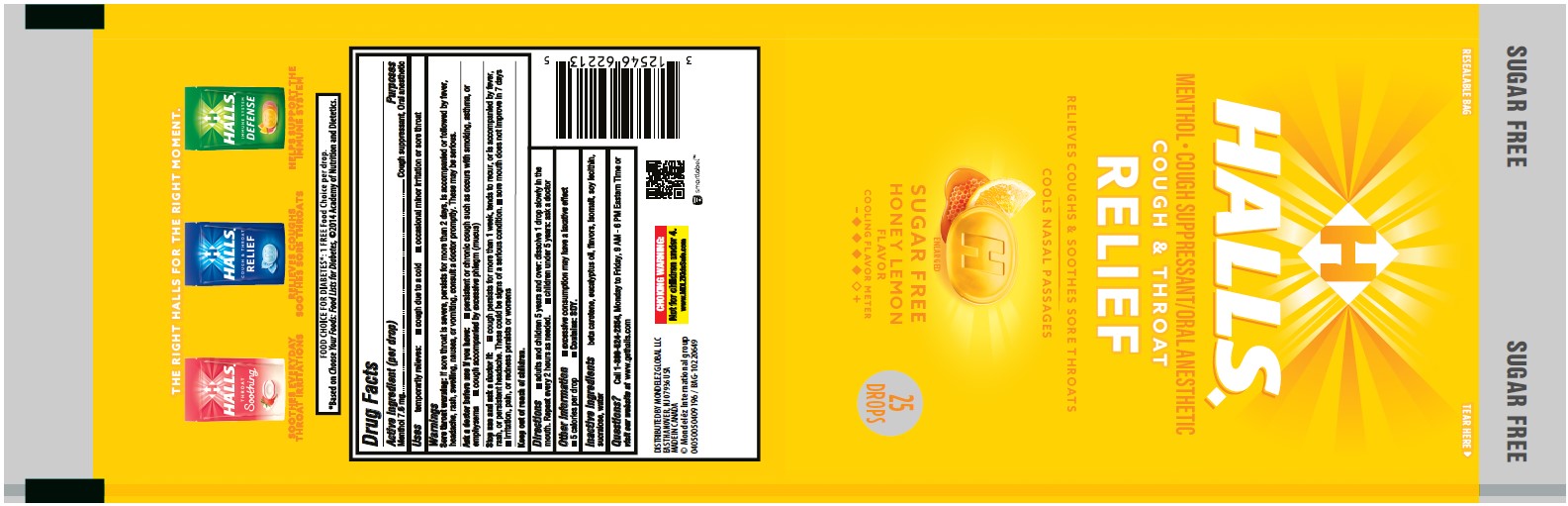 DRUG LABEL: Halls
NDC: 12546-642 | Form: LOZENGE
Manufacturer: Mondelez Global LLC
Category: otc | Type: HUMAN OTC DRUG LABEL
Date: 20251006

ACTIVE INGREDIENTS: MENTHOL 7.6 mg/1 1
INACTIVE INGREDIENTS: .BETA.-CAROTENE; EUCALYPTUS OIL; ISOMALT; LECITHIN, SOYBEAN; SUCRALOSE; WATER

Halls SF honey lemon bag

Active Ingredient

<(per drop) Menthol 7.6 mg>

Purposes

<Cough Suppressant, Oral Anesthetic>

Uses

<temporarily relieves:

- cough due to a cold
- occasional minor irritation or sore throat>

Warnings

<Sore throat warnings: if sore throat is severe, persist for more than 2 days, is accompanied or followed by fever, headache, rash, swelling, nausea, or vomiting, consult a doctor promptly. These may be serious.>

Ask a doctor before use if you have

- persistent or chronic cough such as occurs with smoking, asthma, or emphysema
- cough accompanied by excessive phlegm (mucus)

Stop use and ask a doctor if

- cough persists for more than 1 week, tends to recur, or is accompanied by fever, rash, or persistent headache. These could be signs of a serious condition.
- sore mouth does not improve in 7 days
- irritation, pain, or redness persists or worsens

Keep out of reach of children.

Enter section text here

Directions

- adults and children 5 years and over: dissolve 1 drop slowly in the mouth. Repeat every 2 hours as needed.
- children under 5 years: ask a doctor

Other information

- excessive consumption may have a laxative effect
- 5 calories per drop
- Contains: SOY

Inactive ingredients

<beta carotene, eucalyptus oil, flavors, isomalt, soy lecithin, sucralose, water>

Questions?

<Call 1-800-524-2854, Monday to Friday, 9 AM - 6 PM Eastern Time or visit our website at www.gethalls.com>